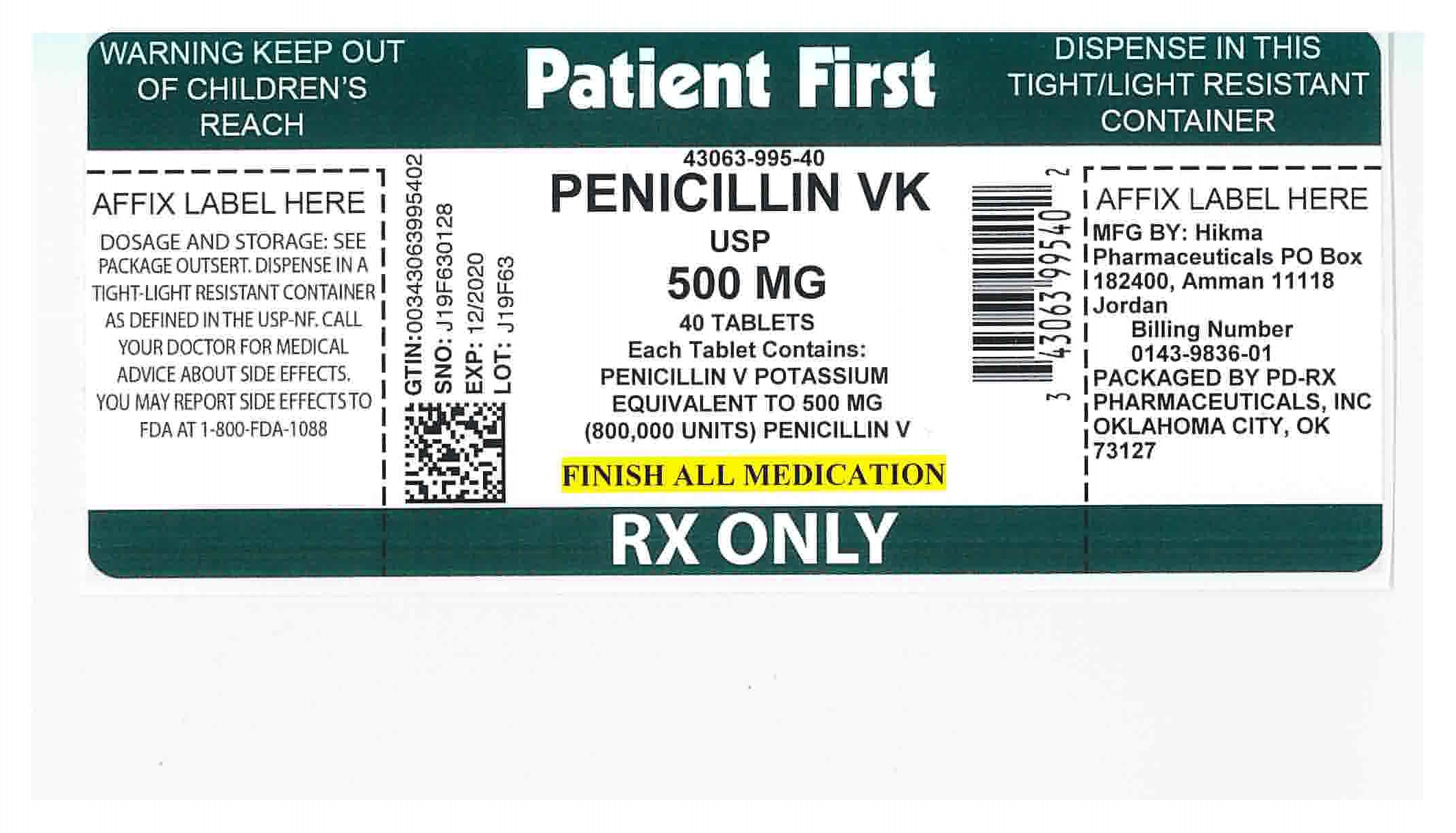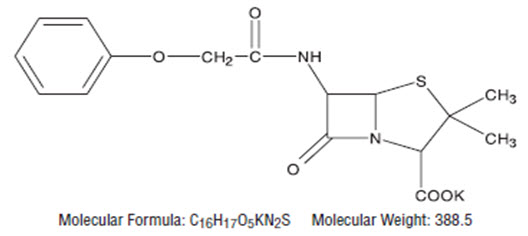 DRUG LABEL: Penicillin V Potassium
NDC: 43063-995 | Form: TABLET, FILM COATED
Manufacturer: PD-Rx Pharmaceuticals, Inc.
Category: prescription | Type: HUMAN PRESCRIPTION DRUG LABEL
Date: 20251017

ACTIVE INGREDIENTS: PENICILLIN V POTASSIUM 500 mg/1 1
INACTIVE INGREDIENTS: HYPROMELLOSES; MAGNESIUM STEARATE; POLYETHYLENE GLYCOL, UNSPECIFIED; POVIDONE; TALC; TITANIUM DIOXIDE; CELLULOSE, MICROCRYSTALLINE

Penicillin V Potassium Tablets

250 mg (400,000 Units)
500 mg (800,000 Units)

Rx Only

To reduce the development of drug-resistant bacteria and maintain the effectiveness of penicillin V potassium tablets and other antibacterial drugs, penicillin V potassium tablets should be used only to treat or prevent infections that are proven or strongly suspected to be caused by bacteria.

DESCRIPTION

Penicillin V is the phenoxymethyl analog of penicillin G.
Penicillin V potassium is the potassium salt of penicillin V.

Penicillin V Potassium Tablets, USP for oral administration contain penicillin V potassium equivalent to 250 mg (400,000 units) or 500 mg (800,000 units) penicillin V. In addition, each tablet contains the following inactive ingredients: hydroxypropyl methylcellulose, magnesium stearate, polyethylene glycol, povidone, talc, titanium dioxide and microcrystalline cellulose.

CLINICAL PHARMACOLOGY

Penicillin V exerts a bactericidal action against penicillin-sensitive microorganisms during the stage of active multiplication. It acts through the inhibition of biosynthesis of cell-wall mucopeptide. It is not active against the penicillinase-producing bacteria, which include many strains of staphylococci. The drug exerts high in vitroactivity against staphylococci (except penicillinase-producing strains), streptococci (groups A, C, G, H, L and M), and pneumococci. Other organisms sensitive in vitroto penicillin V are Corynebacterium diphtheriae, Bacillus anthracis, Clostridia, Actinomyces bovis, Streptobacillus moniliformis, Listeria monocytogenes, Leptospira,and Neisseria gonorrhoeae. Treponema pallidumis extremely sensitive.

The potassium salt of penicillin V has the distinct advantage over penicillin G in resistance to inactivation by gastric acid. It may be given with meals; however, blood levels are slightly higher when the drug is given on an empty stomach. Average blood levels are two to five times higher than the levels following the same dose of oral penicillin G and also show much less individual variation.

Once absorbed, penicillin V is about 80% bound to serum protein. Tissue levels are highest in the kidneys, with lesser amounts in the liver, skin, and intestines. Small amounts are found in all other body tissues and the cerebrospinal fluid. The drug is excreted as rapidly as it is absorbed in individuals with normal kidney function; however, recovery of the drug from the urine indicates that only about 25% of the dose given is absorbed. In neonates, young infants, and individuals with impaired kidney function, excretion is considerably delayed.

MICROBIOLOGY

Susceptibility Testing

For specific information regarding susceptibility test interpretive criteria and associated test methods and quality control standards recognized by FDA for this drug, please see: https://www.fda.gov/STIC.

INDICATIONS AND USAGE

Penicillin V Potassium Tablets are indicated in the treatment of mild to moderately severe infections due to penicillin G-sensitive microorganisms. Therapy should be guided by bacteriological studies (including sensitivity tests) and by clinical response.

NOTE: Severe pneumonia, empyema, bacteremia, pericarditis, meningitis, and arthritis should not be treated with penicillin V during the acute stage. Indicated surgical procedures should be performed.

The following infections will usually respond to adequate dosage of penicillin V.

Streptococcal Infections (without bacteremia)
Mild-to-moderate infections of the upper respiratory tract, scarlet fever, and mild erysipelas.

NOTE: Streptococci in groups A, C, G, H, L, and M are very sensitive to penicillin.
Other groups, including group D (enterococcus), are resistant.

Pneumococcal Infections
Mild to moderately severe infections of the respiratory tract.

Staphylococcal infections – penicillin G-sensitive
Mild infections of the skin and soft tissues.

NOTE: Reports indicate an increasing number of strains of staphylococci resistant to penicillin G, emphasizing the need for culture and sensitivity studies in treating suspected staphylococcal infections.

Fusospirochetosis (Vincent's gingivitis and pharyngitis)
Mild to moderately severe infections of the oropharynx usually respond to therapy with oral penicillin.

NOTE: Necessary dental care should be accomplished in infections involving the gum tissue.

Medical conditions in which oral penicillin therapy is indicated as prophylaxis: For the prevention of recurrence following rheumatic fever and/or chorea: Prophylaxis with oral penicillin on a continuing basis has proven effective in preventing recurrence of these conditions.

Although no controlled clinical efficacy studies have been conducted, penicillin V has been suggested by the American Heart Association and the American Dental Association for use as an oral regimen for prophylaxis against bacterial endocarditis in patients who have congenital heart disease or rheumatic or other acquired valvular heart disease when they undergo dental procedures and surgical procedures of the upper respiratory tract^1. Oral penicillin should not be used in those patients at particularly high risk for endocarditis (e.g., those with prosthetic heart valves or surgically constructed systemic pulmonary shunts). Penicillin V should not be used as adjunctive prophylaxis for genitourinary instrumentation or surgery, lower-intestinal tract surgery, sigmoidoscopy, and childbirth. Since it may happen that alphahemolytic streptococci relatively resistant to penicillin may be found when patients are receiving continuous oral penicillin for secondary prevention of rheumatic fever, prophylactic agents other than penicillin may be chosen for these patients and prescribed in addition to their continuous rheumatic fever prophylactic regimen.

NOTE: When selecting antibiotics for the prevention of bacterial endocarditis, the physician or dentist should read the full joint statement of the American Heart Association and the American Dental Association^1.

To reduce the development of drug-resistant bacteria and maintain the effectiveness of Penicillin V Potassium Tablets and other antibacterial drugs, Penicillin V Potassium Tablets should be used only to treat or prevent infections that are proven or strongly suspected to be caused by susceptible bacteria. When culture and susceptibility information are available, they should be considered in selecting or modifying antibacterial therapy. In the absence of such data, local epidemiology and susceptibility patterns may contribute to the empiric selection of therapy.

CONTRAINDICATIONS

A previous hypersensitivity reaction to any penicillin is a contraindication.

WARNINGS

SERIOUS AND OCCASIONALLY FATAL HYPERSENSITIVITY (anaphylactic) REACTIONS HAVE BEEN REPORTED IN PATIENTS ON PENICILLIN THERAPY. THESE REACTIONS ARE MORE LIKELY TO OCCUR IN INDIVIDUALS WITH A HISTORY OF PENICILLIN HYPERSENSITIVITY AND/OR A HISTORY OF SENSITIVITY TO MULTIPLE ALLERGENS. THERE HAVE BEEN REPORTS OF INDIVIDUALS WITH A HISTORY OF PENICILLIN HYPERSENSITIVITY WHO HAVE EXPERIENCED SEVERE REACTIONS WHEN TREATED WITH CEPHALOSPORINS. BEFORE INITIATING THERAPY WITH PENICILLIN V POTASSIUM TABLETS, CAREFUL INQUIRY SHOULD BE MADE CONCERNING PREVIOUS HYPERSENSITIVITY REACTIONS TO PENICILLINS, CEPHALOSPORINS, OR OTHER ALLERGENS. IF AN ALLERGIC REACTION OCCURS, PENICILLIN V POTASSIUM TABLETS SHOULD BE DISCONTINUED AND APPROPRIATE THERAPY INSTITUTED. SERIOUS ANAPHYLACTIC REACTIONS REQUIRE IMMEDIATE EMERGENCY TREATMENT WITH EPINEPHRINE. OXYGEN, INTRAVENOUS STEROIDS, AND AIRWAY MANAGEMENT, INCLUDING INTUBATION, SHOULD ALSO BE ADMINISTERED AS INDICATED.

Clostridiumdifficileassociated diarrhea (CDAD) has been reported with use of nearly all antibacterial agents, including penicillin and may range in severity from mild diarrhea to fatal colitis. Treatment with antibacterial agents alters the normal flora of the colon leading to overgrowth of C. difficile.

C. difficileproduces toxins A and B which contribute to the development of CDAD. Hypertoxin producing strains of C. difficilecause increased morbidity and mortality, as these infections can be refractory to antimicrobial therapy and may require colectomy. CDAD must be considered in all patients who present with diarrhea following antibiotic use. Careful medical history is necessary since CDAD has been reported to occur over two months after the administration of antibacterial agents.

If CDAD is suspected or confirmed, ongoing antibiotic use not directed against C. difficilemay need to be discontinued. Appropriate fluid and electrolyte management, protein supplementation, antibiotic treatment of C. difficile,and surgical evaluation should be instituted as clinically indicated.

PRECAUTIONS

Penicillin tablets should be used with caution in individuals with histories of significant allergies and/or asthma.

General

Prescribing penicillin V potassium tablets in the absence of a proven or strongly suspected bacterial infection or a prophylactic indication is unlikely to provide benefit to the patient and increases the risk of the development of drug-resistant bacteria.

The oral route of administration should not be relied upon in patients with severe illness, or with nausea, vomiting, gastric dilatation, cardiospasm, or intestinal hypermotility.

Occasional patients will not absorb therapeutic amounts of orally administered penicillin.

In streptococcal infections, therapy must be sufficient to eliminate the organism (10-day minimum); otherwise the sequelae of streptococcal disease may occur. Cultures should be taken following completion of treatment to determine whether streptococci have been eradicated.

Prolonged use of antibiotics may promote the overgrowth of nonsusceptible organisms, including fungi. Should superinfection occur, appropriate measures should be taken.

Information for Patients

Patients should be counseled that antibacterial drugs including penicillin V potassium tablets should only be used to treat bacterial infections. They do not treat viral infections (e.g., the common cold). When penicillin V potassium tablets are prescribed to treat a bacterial infection, patients should be told that although it is common to feel better early in the course of therapy, the medication should be taken exactly as directed. Skipping doses or not completing the full course of therapy may: (1) decrease the effectiveness of the immediate treatment, and (2) increase the likelihood that bacteria will develop resistance and will not be treatable by penicillin V potassium tablets or other antibacterial drugs in the future.

Diarrhea is a common problem caused by antibiotics which usually ends when the antibiotic is discontinued. Sometimes after starting treatment with antibiotics, patients can develop watery and bloody stools (with or without stomach cramps and fever) even as late as two or more months after having taken the last dose of the antibiotic. If this occurs, patients should contact their physician as soon as possible.

ADVERSE REACTIONS

Although the incidence of reactions to oral penicillins has been reported with much less frequency than following parenteral therapy, it should be remembered that all degrees of hypersensitivity, including fatal anaphylaxis, have been reported with oral penicillin.

The most common reactions to oral penicillin are nausea, vomiting, epigastric distress, diarrhea, and black hairy tongue. The hypersensitivity reactions reported are skin eruptions (maculopapular to exfoliative dermatitis), urticaria and other serum-sickness like reactions, laryngeal edema, and anaphylaxis.

Fever and eosinophilia may frequently be the only reaction observed. Hemolytic anemia, leukopenia, thrombocytopenia, neuropathy, and nephropathy are infrequent reactions and usually associated with high doses of parenteral penicillin.

To report SUSPECTED ADVERSE REACTIONS, contact Hikma Pharmaceuticals USA Inc. at 1-877-233-2001, or FDA at 1-800-FDA-1088 or www.fda.gov/medwatch.

DOSAGE AND ADMINISTRATION

The dosage of penicillin V potassium tablets should be determined according to the sensitivity of the causative microorganisms and the severity of infection, and adjusted to the clinical response of the patient.

The usual dosage recommendations for adults and children 12 years and over are as follows:

Streptococcal Infections
Mild to moderately severe - of the upper respiratory tract and including scarlet fever and erysipelas: 125 to 250 mg (200,000 to 400,000 units) every 6 to 8 hours for 10 days.

Pneumococcal Infections
Mild to moderately severe - of the respiratory tract, including otitis media: 250 to 500 mg (400,000 to 800,000 units) every 6 hours until the patient has been afebrile for at least 2 days.

Staphylococcal Infections
Mild infections of skin and soft tissue (culture and sensitive tests should be performed): 250 to 500 mg (400,000 to 800,000 units) every 6 to 8 hours.

Fusospirochetosis (Vincent's infection) of the oropharynx.
Mild to moderately severe infections: 250 to 500 mg (400,000 to 800,000 units) every 6 to 8 hours.

For the prevention of recurrence following rheumatic fever and/or chorea: 125 to 250 mg (200,000 to 400,000 units) twice daily on a continuing basis.

For prophylaxis against bacterial endocarditis^1in patients with congenital heart disease or rheumatic or other acquired valvular heart disease when undergoing dental procedures or surgical procedures of the upper respiratory tract: 2 gram of penicillin V (1 gram for children under 60 lbs.) 1 hour before the procedure, and then, 1 gram (500 mg for children under 60 lbs.) 6 hours later.

HOW SUPPLIED

Penicillin V Potassium Tablets, USP 500 mg (800,000 units) are white modified capsule shaped film coated tablets bisected from both sides and engraved with “W” on one side of the bisect and “112” on the other side.

Bottles of 28 NDC 43063-995-28

Bottles of 40 NDC 43063-995-40

Store at 20° to 25°C (68° to 77°F) [See USP Controlled Room Temperature].

Keep container tightly closed. Dispense in a tight, light-resistant container, as defined in the USP using a child-resistant closure.

REFERENCES

1. American Heart Association.1984. Prevention of bacterial endocarditis. Circulation 70(6):1123A –1127A.

Distributed by:
Hikma Pharmaceuticals USA Inc.
Berkeley Heights, NJ 07792

Manufactured by:
HIKMA Pharmaceuticals
P.O. Box 182400
Amman 11118 - Jordan

2INPPSMTB

Revised January 2024

PACKAGE LABEL

Penicillin V Potassium Tablets, USP
500 mg (800,000 Units)